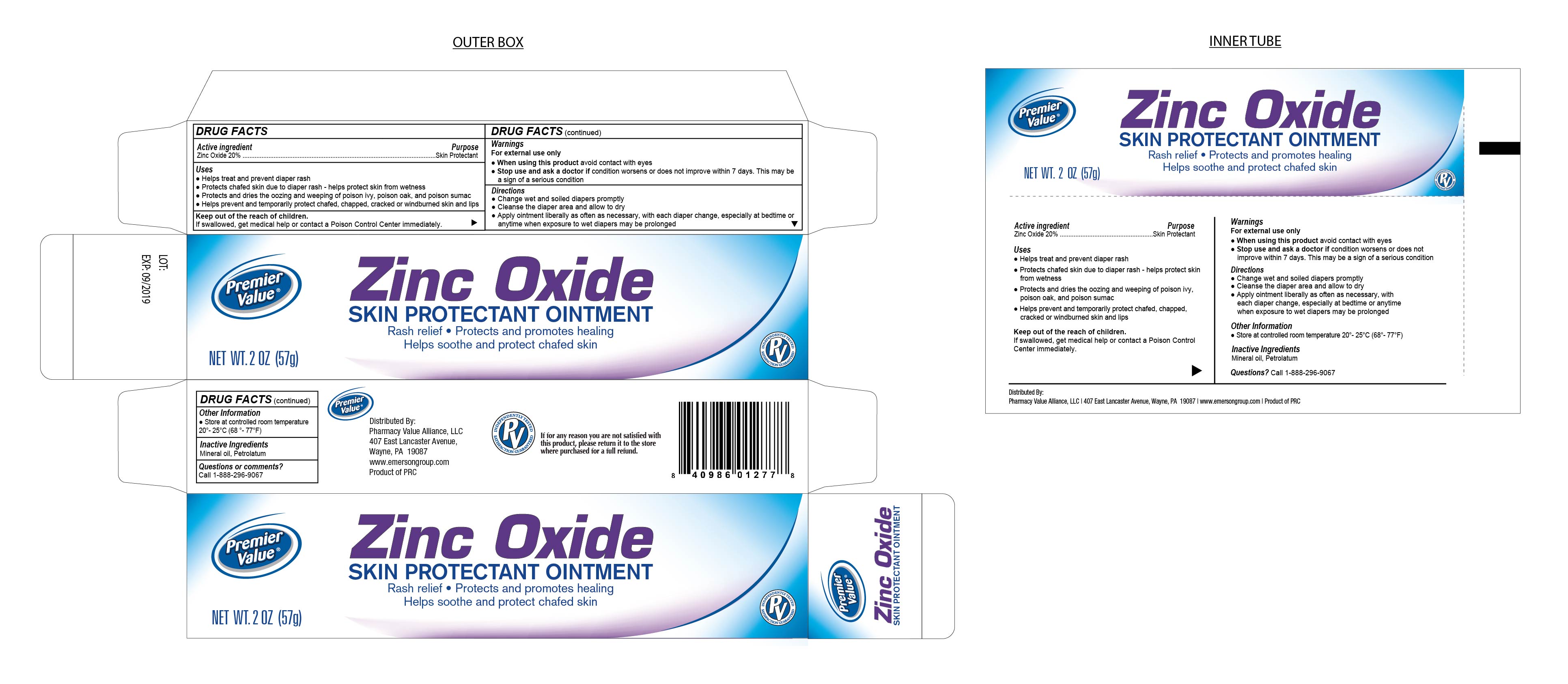 DRUG LABEL: Zinc Oxide 20%
NDC: 68016-159 | Form: OINTMENT
Manufacturer: Pharmacy Value Alliance, LLC
Category: otc | Type: HUMAN OTC DRUG LABEL
Date: 20241220

ACTIVE INGREDIENTS: ZINC OXIDE 0.2 g/1 g
INACTIVE INGREDIENTS: MINERAL OIL; PETROLATUM

Zinc Oxide Ointment 20%

Active Ingredient

Zinc Oxide 20%

Purpose

Skin Protectant

Uses

- Helps treat and prevent diaper rash
- Protects chafed skin due to diaper rash - helps protect skin from wetness
- Protects and dries the oozing and weeping of poison ivy, poison oak and poison sumac
- Helps prevent and temporarily protect chafed, chapped, cracked or windburned skin and lips

Keep out of the reach of children

If swallowed, get medical help or contact a Poison Control Center immediately.

Warnings

For External Use Only

- When using this product avoid contact with eyes
- Stop use and ask a doctor if condition worsens or does not improve within 7 days. This may be a sign of a serious condition.

Directions

- Change wet and soiled diapers promptly
- Cleanse the diaper area and allow to dry
- Apply ointment liberally as often as necessary. With each diaper change, especially at betime or anytime when exposure to wet diapers may be prolonged

Other Information

- Store at controlled room temperature 20° - 25°C (68° - 77°F)

Inactive Ingredients

Mineral Oil, Petrolatum

Distributed By:

Pharmacy Value Alliance, LLC.

407 East Lancaster Avenue, Wayne, PA. 19087

www.emersongroup.com

Product of PRC